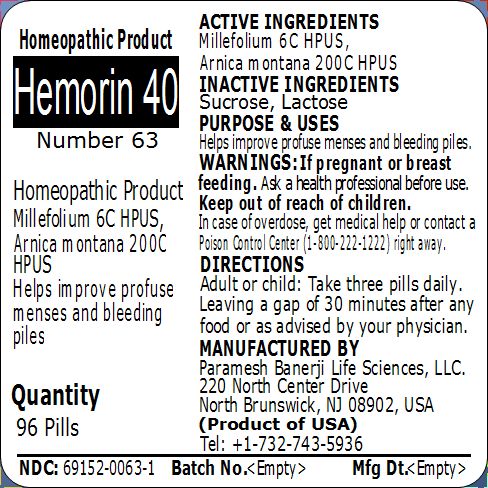 DRUG LABEL: Hemorin 40 (Number 63)
NDC: 69152-0063 | Form: PELLET
Manufacturer: Paramesh Banerji Life Sciences LLC
Category: homeopathic | Type: HUMAN OTC DRUG LABEL
Date: 20150309

ACTIVE INGREDIENTS: ACHILLEA MILLEFOLIUM 6 [hp_C]/1 1; ARNICA MONTANA 200 [hp_C]/1 1
INACTIVE INGREDIENTS: SUCROSE; LACTOSE

Active Ingredients

Millefolium 6C HPUS, Arnica montana 200C HPUS

Inactive Ingredients

Sucrose, Lactose

Purpose

Helps improve profuse menses and bleeding piles

Uses

Helps improve profuse menses and bleeding piles

Warnings

If pregnant or breast feeding ask a health professional before use.

Keep out of reach of children. In case of overdose, get medical help or contact a Poison Control Center (1-800-222-1222) right away.

Direction

Adult or child: Take three pills daily. Leaving a gap of 30 minutes after any food or as advised by your physician.

Manufactured by

Paramesh Banerji Life Sciences, LLC

220 North Center Drive

North Brunswick, NJ 08902, USA

Product of USA

Tel: +1-732-743-5936

Principal Display Panel

Homeopathic Product

Hemorin 40

Number 63

Homeopathic Product

Millefolium 6C HPUS, Arnica montana 200C HPUS

Helps improve profuse menses and bleeding piles

Quantity

96 Pills